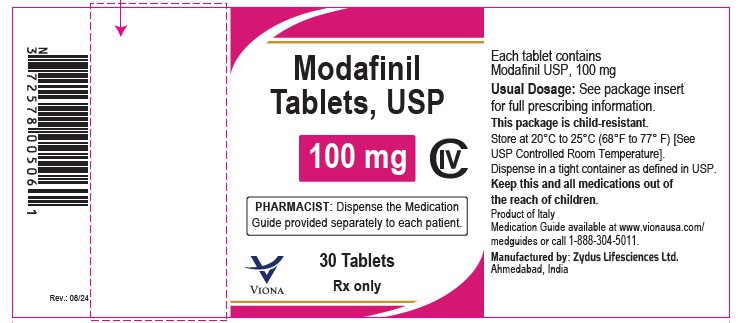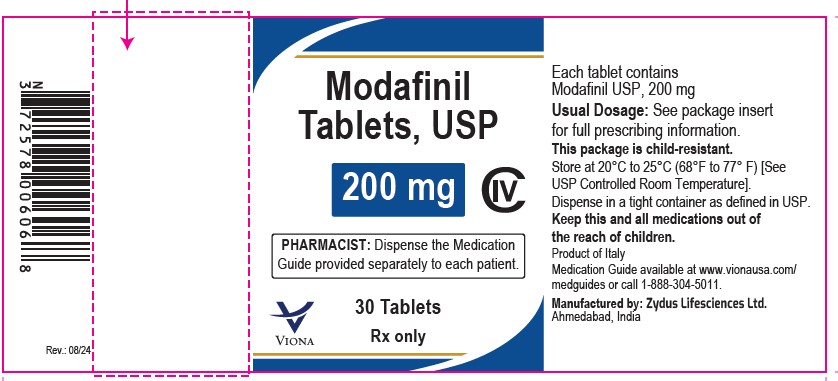 DRUG LABEL: Modafinil
NDC: 70771-1051 | Form: TABLET
Manufacturer: Zydus Lifesciences Limited
Category: prescription | Type: HUMAN PRESCRIPTION DRUG LABEL
Date: 20240816
DEA Schedule: CIV

ACTIVE INGREDIENTS: MODAFINIL 100 mg/1 1
INACTIVE INGREDIENTS: CELLULOSE, MICROCRYSTALLINE; CROSCARMELLOSE SODIUM; LACTOSE MONOHYDRATE; MAGNESIUM STEARATE; POVIDONE; STARCH, CORN

MODAFINIL TABLETS CIV

PACKAGE LABEL.PRINCIPAL DISPLAY PANEL

NDC 70771-1051-3

Modafinil Tablets USP, 100 mg

30 Tablets

Rx only

NDC 70771-1052-3

Modafinil Tablets USP, 200 mg

30 Tablets

Rx only